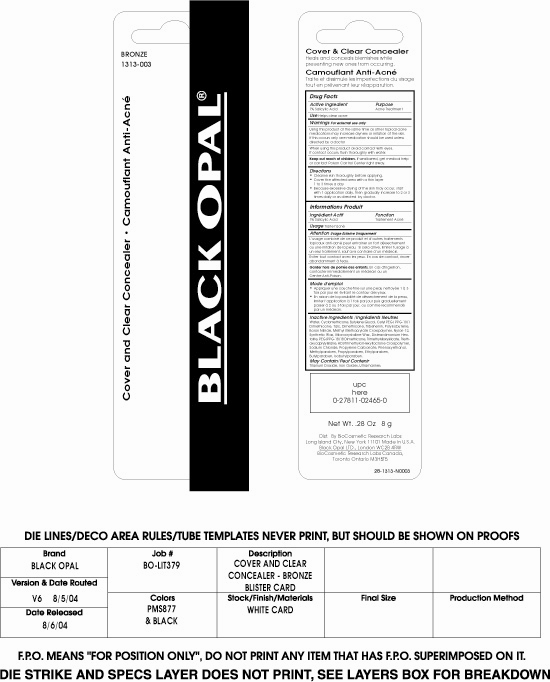 DRUG LABEL: Cover and Conceal Blemish Concealer
NDC: 59735-300 | Form: CREAM
Manufacturer: Biocosmetics research labs
Category: otc | Type: HUMAN OTC DRUG LABEL
Date: 20100415

ACTIVE INGREDIENTS: Salicylic Acid 1 g/100 g

Blemish concealer package label

Active Ingredient:

Salicylic Acid 1%

Purpose

Acne Treatment

INDICATIONS AND USAGE

Use Helps clear acne

Warnings For external use only

DRUG INTERACTIONS

Using this product at the same time as other topical acne medications may increase dryness or irritation of the skin. If this occurs only one medication should be used unless directed by a doctor.

When using this product avoid contact with eyes
If contact occurs, flush thoroughly with water

Keep out of reach of Children

If swallowed get medical help or contact Poison Control Center right away.

DOSAGE AND ADMINISTRATION

- Cleanse skin thoroughly before applying
- Cover the affected area with a thin layer 1 to 3 times a day
- Because excessive drying of the skin may occur, start with 1 application daily, then gradually increase to 2 or 3 times daily or as directed by doctor

Inactive Ingredients
Water, Cyclomethicone, Butylene Glycol, Cetyl PEG/PPG-10/1 Dimethicone, Talc, Dimethicone, Tribehenin, Polyisobutene, Boron Nitride, Methyl Methacrylate Crosspolymer, Nylon-12, Synthetic Wax, Microcrystalline Wax, Disteardimonium Hectorite, PEG/PPG-18/18 Dimethicone, Trimethylsiloxysilicate, Triethoxycaprylylsilane, HDI/Trimethylol Hexyllactone Crosspolymer, Sodium Chloride, Propylene Carbonate, Phenoxyethanol, Methylparaben, Propylparaben, Ethylparaben, Butylparaben, Isobutylparaben
May contain
Titanium Dioxide, Iron Oxides

PACKAGE LABEL

Enter section text here